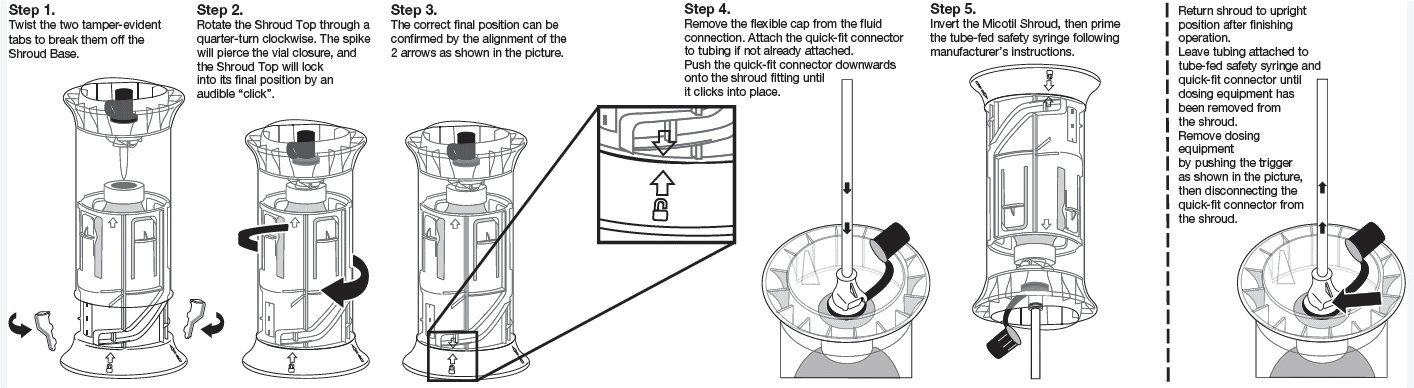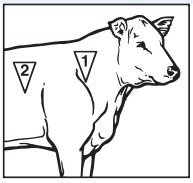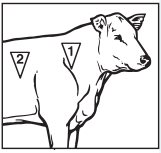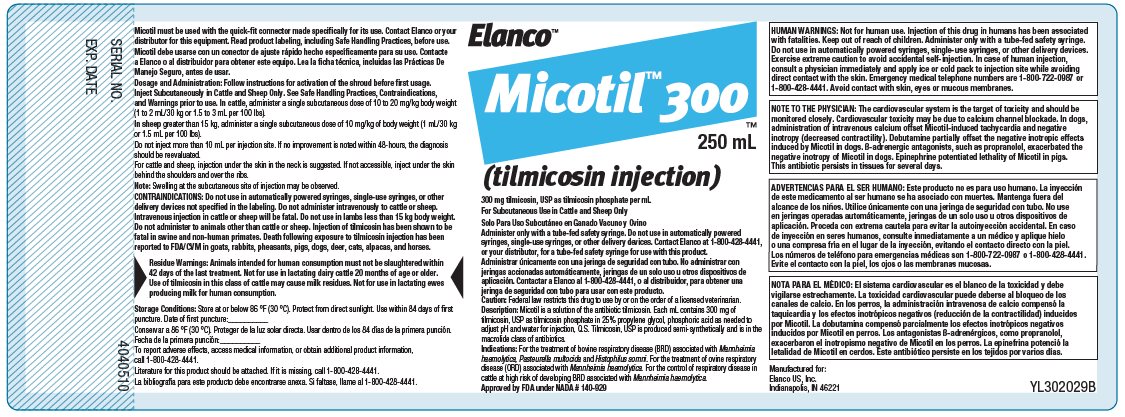 DRUG LABEL: Micotil 300
NDC: 58198-0230 | Form: INJECTION
Manufacturer: Elanco US Inc.
Category: animal | Type: PRESCRIPTION ANIMAL DRUG LABEL
Date: 20251029

ACTIVE INGREDIENTS: tilmicosin phosphate 300 mg/1 mL

Approved by FDA under NADA # 140-929

Micotil™ 300

(tilmicosin injection)

300 mg tilmicosin, USP as tilmicosin phosphate per mL
For Subcutaneous Use in Cattle and Sheep Only
Solo Para Uso Subcutáneo en Ganado Vacuno y Ovino

Caution: Federal law restricts this drug to use by or on the order of a licensed veterinarian.

HUMAN WARNINGS: Not for human use. Injection of this drug in humans has been associated with fatalities. Keep out of reach of children. Administer only with a tube-fed safety syringe. Do not use in automatically powered syringes, single-use syringes, or other delivery devices. Exercise extreme caution to avoid accidental self-injection. In case of human injection, consult a physician immediately and apply ice or cold pack to injection site while avoiding direct contact with the skin. Emergency medical telephone numbers are 1-800-722-0987 or 1-800-428-4441. Avoid contact with skin, eyes, or mucous membranes.

NOTE TO THE PHYSICIAN: The cardiovascular system is the target of toxicity and should be monitored closely. Cardiovascular toxicity may be due to calcium channel blockade. In dogs, administration of intravenous calcium offset Micotil-induced tachycardia and negative inotropy (decreased contractility). Dobutamine partially offset the negative inotropic effects induced by Micotil in dogs. ß-adrenergic antagonists, such as propranolol, exacerbated the negative inotropy of Micotil in dogs. Epinephrine potentiated lethality of Micotil in pigs. This antibiotic persists in tissues for several days.

ADVERTENCIAS PARA EL SER HUMANO: Este producto no es para uso humano. La inyección de este medicamento al ser humano se ha asociado con muertes. Mantenga fuera del alcance de los niños. Utilice únicamente con una jeringa de seguridad con tubo. No use en jeringas operadas automáticamente, jeringas de un solo uso u otros dispositivos de aplicación. Proceda con extrema cautela para evitar la autoinyección accidental. En caso de inyección en seres humanos, consulte inmediatamente a un médico y aplique hielo o una compresa fría en el lugar de la inyección, evitando el contacto directo con la piel. Los números de teléfono para emergencias médicas son 1-800-722-0987 o 1-800-428-4441. Evite el contacto con la piel, los ojos o las membranas mucosas.

NOTA PARA EL MÉDICO: El sistema cardiovascular es el blanco de la toxicidad y debe vigilarse estrechamente. La toxicidad cardiovascular puede deberse al bloqueo de los canales de calcio. En los perros, la administración intravenosa de calcio compensó la taquicardia y los efectos inotrópicos negativos (reducción de la contractilidad) inducidos por Micotil (tilmicosina inyectable). La dobutamina compensó parcialmente los efectos inotrópicos negativos inducidos por Micotil en perros. Los antagonistas ß-adrenérgicos, como propranolol, exacerbaron el inotropismo negativo de Micotil en los perros. La epinefrina potenció la letalidad de Micotil en cerdos. Este antibiótico persiste en los tejidos por varios días.

Description:

Micotil (tilmicosin injection) is a solution of the antibiotic tilmicosin. Each mL contains 300 mg of tilmicosin, USP as tilmicosin phosphate in 25% propylene glycol, phosphoric acid as needed to adjust pH and water for injection, Q.S. Tilmicosin, USP is produced semi-synthetically and is in the macrolide class of antibiotics.

Indications:

Micotil is indicated for the treatment of bovine respiratory disease (BRD) associated with Mannheimia haemolytica, Pasteurella multocida and Histophilus somni and for the treatment of ovine respiratory disease (ORD) associated with Mannheimia haemolytica. Micotil is indicated for the control of respiratory disease in cattle at high risk of developing BRD associated with Mannheimia haemolytica.

Dosage and Administration:

Follow instructions for activation of the shroud before first usage.

Inject Subcutaneously in Cattle and Sheep Only. See Safe Handling Practices, Contraindications, and Warnings prior to use. In cattle, administer a single subcutaneous dose of 10 to 20 mg/kg of body weight (1 to 2 mL/30 kg or 1.5 to 3 mL per 100 lbs). In sheep greater than 15 kg, administer a single subcutaneous dose of 10 mg/kg of body weight (1 mL/30 kg or 1.5 mL per 100 lbs). Do not inject more than 10 mL per injection site.

If no improvement is noted within 48-hours, the diagnosis should be reevaluated.

For cattle and sheep, injection under the skin in the neck is suggested. If not accessible, inject under the skin behind the shoulders and over the ribs.

Note: Swelling at the subcutaneous site of injection may be observed.

Contraindications:

Do not use in automatically powered syringes, single-use syringes, or other delivery devices not specified in the labeling. Do not administer intravenously to cattle or sheep. Intravenous injection in cattle or sheep will be fatal. Do not use in lambs less than 15 kg body weight. Do not administer to animals other than cattle or sheep. Injection of tilmicosin has been shown to be fatal in swine and non-human primates. Death following exposure to tilmicosin injection has been reported to FDA/CVM in goats, rabbits, pheasants, pigs, dogs, deer, cats, alpacas and horses.

Warnings:

Residue Warnings: Animals intended for human consumption must not be slaughtered within 42 days of the last treatment. Not for use in lactating dairy cattle 20 months of age or older. Use of tilmicosin in this class of cattle may cause milk residues. Not for use in lactating ewes producing milk for human consumption.

For Subcutaneous Use in Cattle and Sheep Only. Administer only with a tube-fed safety syringe. Do not use in automatically powered syringes, single-use syringes, or other delivery devices. Contact Elanco at 1-800-428-4441, or your distributor, for a tube-fed safety syringe for use with this product.

Solo Para Uso Subcutáneo en Ganado Vacuno y Ovino. Administrar únicamente con una jeringa de seguridad con tubo. No administrar con jeringas accionadas automáticamente, jeringas de un solo uso u otros dispositivos de aplicación. Contactar a Elanco al 1-800-428-4441, o al distribuidor, para obtener una jeringa de seguridad con tubo para usar con este producto.

Precautions:

The effects of tilmicosin on bovine and ovine reproductive performance, pregnancy and lactation have not been determined. Intramuscular injection will cause a local reaction which may result in trim loss of edible tissue at slaughter.

Adverse Reactions:

The following adverse reactions have been reported post-approval: In cattle: injection site swelling and inflammation, lameness, collapse, anaphylaxis/anaphylactoid reactions, decreased food and water consumption, and death.

In sheep: dyspnea and death.

For additional information about reporting adverse drug experiences for animal drugs, contact FDA at 1-888-FDA-VETS or http://www.fda.gov/reportanimalae

Clinical Pharmacology:

A single subcutaneous injection of Micotil (tilmicosin injection) at 10 mg/kg of body weight dose in cattle resulted in peak tilmicosin levels within one hour and detectable levels (0.07 μg/mL) in serum beyond 3 days. However, lung concentrations of tilmicosin remained above the tilmicosin MIC 95% of 3.12 μg/mL for Mannheimia haemolytica for at least 3 days following the single injection. Serum tilmicosin levels are a poor indicator of total body tilmicosin. The lung/serum tilmicosin ratio in favor of lung tissue appeared to equilibrate by 3 days post-injection at approximately 60. In a study with radioactive tilmicosin, 24% and 68% of the dose was recovered from urine and feces respectively over 21 days. After a single subcutaneous injection of Micotil at 10 mg/kg of body weight, tilmicosin concentrations in excess of 4 μg/mL were maintained in the alveolar macrophages and neutrophils of most cattle for at least 10 days. The clinical relevance of these findings has not been determined.

Microbiology:

Tilmicosin has an in vitro antibacterial spectrum that is predominantly Gram-positive with activity against certain Gram-negative microorganisms. In vitro activity against several Mycoplasma species has also been observed.

Effectiveness:

In a multi-location field study, 1508 calves with naturally occurring BRD were treated with Micotil. Responses to treatment were compared to saline-treated controls. A cure was defined as a calf with normal attitude and activity, normal respiration, and a rectal temperature of <104°F on Day 13. The cure rate was significantly higher (P=0.004) in Micotil-treated calves (63.1%) compared to saline-treated calves (29.2%). During the treatment phase of the study, there were 10 BRD-related deaths in the Micotil-treated calves compared to 47 in the saline-treated calves.

Animal Safety:

A safety study was conducted in feeder calves receiving subcutaneous doses of 20, 30, 40, or 60 mg/kg of body weight, injected 3 times at 72-hour intervals. Death was not seen in any of the treatment groups. Injection site swelling and mild hemorrhage at the injection site were seen in animals in all dosage groups. Lesions were described as being generally more severe and occurred at higher frequency rates in the animals treated with higher doses of tilmicosin. Lameness associated with the injection site was noted in two of twenty-four animals (one animal in the 30 mg/kg body weight treatment group and one animal in the 60 mg/kg treatment group). No other drug related lesions were observed macroscopically or microscopically. Decreases in food and water consumption were noted in all treatment groups compared to the control group.

A separate safety study conducted in feeder calves, subcutaneous doses of 10, 30, or 50 mg/kg of body weight, injected 3 times at 72-hour intervals did not cause any deaths. Edema at the site of injection was noted. The only lesion observed at necropsy was minimal myocardial necrosis in some animals dosed at 50 mg/kg.

In an additional safety study, subcutaneous doses of 150 mg/kg body weight injected at 72-hour intervals resulted in death of two of the four treated animals. Edema was marked at the site of injection. Minimal myocardial necrosis was the only lesion observed at necropsy. Deaths of cattle have been observed with a single intravenous dose of 5 mg/kg of body weight.

In sheep, single subcutaneous injections of 10 mg/kg body weight dose did not cause any deaths and no adverse effects of tilmicosin were observed on blood pressure, heart rate, or respiratory rate.

Toxicology:

The heart is the target of toxicity in laboratory and domestic animals given Micotil (tilmicosin injection) by oral or parenteral routes. The primary cardiac effects are increased heart rate (tachycardia) and decreased contractility (negative inotropy). Cardiovascular toxicity may be due to calcium channel blockade.

Upon subcutaneous injection, the acute median lethal dose of tilmicosin in mice is 97 mg/kg, and in rats is 185 mg/kg of body weight. Given orally, the median lethal dose is 800 mg/kg and 2250 mg/kg body weight in fasted and nonfasted rats, respectively.

No compound-related lesions were found at necropsy.

In dogs, intravenous calcium offset Micotil-induced tachycardia and negative inotropy, restoring arterial pulse pressure. Dobutamine partially offset the negative inotropic effects induced by Micotil in dogs.
ß- adrenergic antagonists, such as propranolol, exacerbated the negative inotropy of Micotil in dogs.

In monkeys, a single intramuscular dose of 10 mg/kg body weight caused no signs of toxicity. A single dose of 20 mg/kg body weight caused vomiting and 30 mg/kg body weight caused the death of the only monkey tested.

In swine, intramuscular injection of 10 mg/kg body weight caused increased respiration, emesis, and a convulsion, 20 mg/kg body weight resulted in mortality in 3 of 4 pigs, and 30 mg/kg body weight caused the death of all 4 pigs tested. Injection of 4.5 and 5.6 mg/kg body weight intravenously followed by epinephrine, 1mL (1:1000) intravenously 2 to 6 times, resulted in death of all pigs injected. Pigs given 4.5 mg/kg and 5.6 mg/kg body weight intravenously with no epinephrine all survived.

These results suggest intravenous epinephrine may be contraindicated.

Results of genetic toxicology studies were all negative. Results of teratology and reproduction studies in rats were negative.

The no effect level in dogs after daily oral doses for up to one year is 4 mg/kg of body weight.

Storage Conditions:

Store at or below 86°F (30°C). Protect from direct sunlight. Use within 84 days of first puncture. Store upright between product dispensing. Disconnect and clean dosing equipment for storing as per manufacturer’s instructions.

Conservar a 86 °F (30 °C). Proteger de la luz solar directa. Usar dentro de los 84 días de la primera punción. Guardar en posición vertical entre cada suministro del producto. Desconectar y limpiar el dispositivo de dosificación para el almacenamiento según las instrucciones del fabricante.

How Supplied:

Micotil (tilmicosin injection) is supplied in 250 mL multi-dose amber glass bottles in a non-removable polymer protector.

Manufactured for:

Elanco US, Inc. Indianapolis, IN 46221,
Revised: 08/2025

Micotil, Elanco and the diagonal bar logo are trademarks of Elanco or its affiliates.

© 2025 Elanco or its affiliates

Instructions for Activation of the Shroud

Before first usage activate the shroud-vial-system as shown in the pictures.

Administer only with a tube-fed safety syringe. Do not use in automatically powered syringes, single-use syringes, or other delivery devices. This product must be used with the quick-fit connector made specifically for use with Micotil (tilmicosin injection) that attaches to the shroud fitting. To obtain a tube-fed safety syringe and quick-fit connector, contact Elanco at 1-800- 428-4441, or your distributor.

Micotil should not be stored in dosing equipment. Dosing equipment should be disconnected from the shroud after each use. Store product upright. The dosing equipment should be cleaned according to the manufacturer’s instructions. Avoid contact with skin, eyes, or mucous membranes.

SAFE HANDLING PRACTICES WHEN USING MICOTIL 300 (tilmicosin injection)

Please read this information before you start using Micotil.

This information is a summary and is not intended to take the place of discussions with your veterinarian. Micotil can only be prescribed by a licensed veterinarian who has information specific to your operation. You should discuss with your veterinarian how to use Micotil, human warnings associated with the product and recommended safe handling and use practices. For emergency medical information call 1-800-722-0987 or 1-800-428-4441.

If you have any questions about Micotil, talk with your veterinarian or call Elanco at 1-800-428-4441.

To report an adverse drug event contact Elanco at 1-800-428-4441.

1. WHAT ARE THE POSSIBLE EFFECTS OF ACCIDENTAL HUMAN INJECTION?
Human injections of Micotil have been associated with fatalities. Clinical signs from human exposure include off taste in the mouth, nausea, headache, dizziness, rapid heart rate, chest pain, anxiety, or lightheadedness. Local reactions such as injection site pain, bleeding, swelling or inflammation have been reported.
2. WHAT SHOULD I DO IN THE CASE OF ACCIDENTAL HUMAN INJECTION?
  1. Immediately seek medical attention.
  2. Apply ice or cold pack to injection site, while avoiding direct contact with the skin, and transport immediately to a hospital.
  3. Call 1-800-722-0987 or 1-800-428-4441 for further emergency information.
3. WHAT SHOULD MY PHYSICIAN KNOW IN THE CASE OF ACCIDENTAL HUMAN INJECTION?
  1. The cardiovascular system is the target of toxicity and should be monitored closely.
  2. Cardiovascular toxicity may be due to calcium channel blockade.
  3. Intravenous calcium administration reversed the cardiovascular effects of Micotil in dogs and may provide benefit in patients exhibiting low blood pressure (hypotension) or rapid heart rate (tachycardia).
  4. Dobutamine improved some of the cardiac function in dogs given Micotil.
  5. Epinephrine increased the toxicity of Micotil in pigs, resulting in death.
  6. Propranolol (a beta-adrenergic antagonist) further decreased cardiac function in dogs given Micotil.
  7. The active ingredient in Micotil is tilmicosin phosphate and persists in tissue for several days.
  8. Call 1-800-722-0987 or 1-800-428-4441 for further emergency information.
4. WHAT ARE THE PROPER WAYS TO HANDLE AND STORE MICOTIL?
  1. Store at or below 86°F (30°C), out of direct sunlight, in a safe location, not easily accessible to the general public. Use within 84 days of first puncture. Store upright between product dispensing. Disconnect and clean dosing equipment for storing as per manufacturer’s instructions.
  2. Avoid contact with skin, eyes, or mucous membranes.
  3. Read, understand, and follow all label use directions.
  4. Wash hands thoroughly with soap and water after handling.
5. WHAT ARE THE PROPER METHODS FOR ADMINISTERING MICOTIL?
  1. Properly restrain animals prior to administration.
  2. Work in a team, or if alone, advise someone of your location and how long you plan to be there.
  3. For subcutaneous use. Administer only with a tube-fed safety syringe. Do not use in automatically powered syringes, single-use syringes, or other delivery devices. Contact Elanco at 1-800-428-4441, or your distributor, for a tube-fed safety syringe for use with this product.
  4. Use a 1/2-inch to 5/8-inch, 18- to 16-gauge needle.
  5. With a single hand on the safety syringe insert the needle subcutaneously, at a top-down angle, while avoiding penetration of underlying muscle.
  6. For cattle and sheep, injection under the skin in the neck is suggested. If not accessible, inject under the skin behind the shoulders and over the ribs.
  7. In cattle, administer a single subcutaneous dose of 1.5 to 3.0 mL of Micotil (tilmicosin injection) per 100 lbs of body weight, in either of the two areas noted in the adjacent drawing.
  8. For beef cattle, Beef Quality Assurance recommends injection site 1, unless this site is inaccessible or places the operator in a potentially dangerous situation.
  9. Wash hands thoroughly with soap and water after administration.
  10. Do not administer intravenously (IV) as IV administration will be fatal.
  11. Intramuscular injection will cause a local reaction, which may result in trim loss.
  12. Do not inject more than 10 mL per injection site.
  13. Do not use in lambs less than 15 kg body weight.
6. WHAT ARE SAFE WAYS TO REMOVE AND CHANGE NEEDLES?
  1. Always follow the manufacturer’s instruction of how to safely remove and change needles from the safety syringe.
  2. Plan for the safe handling and disposal of needles before use.
  3. Keep the needle capped until ready to use.
  4. Avoid recapping a used needle.
  5. To safely remove used needles, use tools appropriate for the specific type of safety syringe. Do not remove a used needle with your fingers.
  6. Dispose used needles in an appropriate sharps disposal container. Do not overfill sharps containers and do not put your fingers into a sharps container.
  7. Never place loose needles in household or public trash cans.

PRÁCTICAS DE MANEJO SEGURO CUANDO SE UTILIZA MICOTIL 300 (tilmicosina inyectable)

Lea esta información antes de comenzar a utilizar Micotil. Esta información es un resumen y no pretende sustituir que lo analice con su veterinario. Micotil solamente puede ser prescrito por un médico veterinario autorizado que tenga la información específica de su intervención. Usted deberá analizar con su veterinario cómo usar Micotil, las advertencias para seres humanos asociadas con este producto, y las prácticas de manipulación y uso seguras recomendadas. Para información médica de emergencia, llame al 1-800-722-0987 o 1-800-428-4441. Si tiene alguna pregunta acerca de Micotil, hable con su veterinario o llame a Elanco al teléfono 1-800-428-4441. Para reportar algún evento adverso del medicamento, póngase en contacto con Elanco llamando al 1-800-428-4441.

1. ¿CUÁLES SON LOS POSIBLES EFECTOS DE UNA INYECCIÓN ACCIDENTAL EN UN SER HUMANO?
  Las inyecciones de Micotil al ser humano se asociaron con fallecimientos. Los signos clínicos de la exposición en seres humanos incluyen sabor desagradable en la boca, náuseas, dolor de cabeza, mareos, latidos rápidos, dolor en el pecho, ansiedad o atontamiento. Se han comunicado reacciones locales como dolor, sangrado, tumefacción o inflamación en el sitio de la inyección.
2. ¿QUÉ DEBO HACER EN CASO DE UNA INYECCIÓN ACCIDENTAL A UN SER HUMANO?
  1. Busque atención médica inmediatamente.
  2. Aplique hielo o una compresa fría al sitio de la inyección, evitando el contacto directo con la piel, y transporte al paciente inmediatamente a un hospital.
  3. Llame al 1-800-722-0987 o al 1-800-428-4441 para obtener más información de emergencia.
3. ¿QUÉ DEBE SABER MI MÉDICO EN CASO DE UNA INYECCIÓN ACCIDENTAL A UN SER HUMANO?
  1. El sistema cardiovascular es el blanco de la toxicidad y debe monitorearse estrechamente.
  2. La toxicidad cardiovascular puede deberse a bloqueo de los canales de calcio.
  3. La administración intravenosa de calcio revirtió los efectos cardiovasculares de Micotil (tilmicosina inyectable) en los perros y puede ofrecer beneficios a los pacientes que presentan presión arterial baja (hipotensión) o latidos rápidos (taquicardia).
  4. La dobutamina mejoró parcialmente la función cardíaca en los perros que recibieron Micotil.
  5. La epinefrina aumentó la toxicidad de Micotil en los cerdos, causándoles la muerte.
  6. Propranolol (un antagonista ß-adrenérgico) disminuyó aún más la función cardíaca en perros tratados con Micotil.
  7. El ingrediente activo de Micotil es el fosfato de tilmicosina y persiste en los tejidos por varios días.
  8. Llame al 1-800-722-0987 o al 1-800-428-4441 para obtener más información de emergencia.
4. ¿CUÁLES SON LAS FORMAS ADECUADAS DE MANEJO Y ALMACENAMIENTO DE MICOTIL?
  1. Almacenar a temperatura de 86 °F (30 °C) o menor, fuera de la luz solar directa, en un sitio seguro que no esté fácilmente accesible al público en general. Usar dentro de los 84 días de la primera punción. Guardar en posición vertical entre cada suministro del producto. Desconectar y limpiar el dispositivo de dosificación para el almacenamiento según las instrucciones del fabricante.
  2. Evitar el contacto con la piel, los ojos o las membranas mucosas.
  3. Leer, entender y cumplir con todas las instrucciones para el uso incluidas en la etiqueta.
  4. Lavarse las manos minuciosamente con agua y jabón después de la manipulación.
5. ¿CUÁLES SON LOS MÉTODOS ADECUADOS PARA LA ADMINISTRACIÓN DE MICOTIL?
  1. Sujetar a los animales en forma apropiada antes de la administración.
  2. Trabajar en equipo, o si está solo, informar a alguien de su ubicación y del tiempo que piensa estar allí.
  3. Para uso subcutáneo. Administrar únicamente con una jeringa de seguridad conectada a un tubo. No utilizar jeringas operadas automáticamente, jeringas de un solo uso u otros dispositivos de aplicación. Contactar a Elanco al 1-800-428-4441, o al distribuidor, para obtener una jeringa de seguridad con tubo para usar con este producto.
  4. Utilizar una aguja de 1/2 pulgada a 5/8 de pulgada, del calibre 18 a 16.
  5. Con una sola mano en el dispositivo de dosificación, insertar la aguja subcutáneamente, en un ángulo de arriba hacia abajo, evitando penetrar el músculo subyacente.
  6. Para bovinos y ovinos se recomienda la inyección subcutánea en la región del cuello. Si no fuese accesible, inyectar debajo de la piel detrás de los hombros y sobre las costillas.
  7. En bovinos, administrar una sola dosis subcutánea de 1.5 a 3.0 ml de Micotil por cada 100 libras de peso, en cualquiera de las dos áreas marcadas en el dibujo anexo.
  8. Para el ganado de carne, la Garantía de Calidad de Carne del Bovino recomienda el sitio de inyección 1, a menos que este sitio sea inaccesible o ponga al operador en una situación potencialmente peligrosa.
  9. Lavarse las manos minuciosamente con agua y jabón después de la administración.
  10. No administrar por vía intravenosa (IV) ya que la administración IV causará la muerte.
  11. La inyección intramuscular causará una reacción local, que puede provocar la pérdida de cortes.
  12. No inyectar más de 10 ml por sitio de inyección.
  13. No usar en corderos de menos de 15 kg de peso.
6. ¿CUÁLES SON LAS FORMAS SEGURAS DE RETIRAR Y CAMBIAR LAS AGUJAS?
  1. Seguir siempre las instrucciones del fabricante sobre cómo retirar y cambiar las agujas de la jeringa de seguridad de forma segura.
  2. Planificar la manipulación y eliminación segura de las agujas antes de su uso.
  3. Mantener la aguja tapada hasta el momento de su uso.
  4. Evitar volver a tapar una aguja usada.
  5. Para retirar de forma segura las agujas usadas, utilizar herramientas apropiadas según el tipo específico de jeringa de seguridad. Se debe evitar retirar una aguja usada con los dedos.
  6. Desechar las agujas usadas en un contenedor apropiado para la eliminación de objetos punzantes. No llenar en exceso los contenedores de objetos punzantes y no meter los dedos en dichos contenedores.
  7. No colocar nunca agujas sueltas en los cubos de basura domésticos o públicos.

Micotil, Elanco y el logo de la barra diagonal son marcas de Elanco o sus afiliadas.

Principal Display Panel

Elanco™

Micotil™ 300TM

250 mL

(tilmicosin injection)

300 mg tilmicosin, USP as tilmicosin phosphate per mL

For Subcutaneous Use in Cattle and Sheep Only

Solo Para Uso Subcutáneo en Ganado Vacuno y Ovino